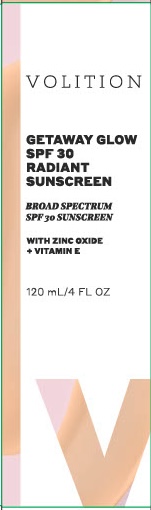 DRUG LABEL: Getaway Glow SPF 30 Radiant Sunscreen
NDC: 72577-101 | Form: LOTION
Manufacturer: Volition Beauty
Category: otc | Type: HUMAN OTC DRUG LABEL
Date: 20260115

ACTIVE INGREDIENTS: ZINC OXIDE 10 g/100 mL
INACTIVE INGREDIENTS: DIETHYLHEXYL 2,6-NAPHTHALATE; HYDROXYETHYL ACRYLATE/SODIUM ACRYLOYLDIMETHYL TAURATE COPOLYMER (45000 MPA.S AT 1%); BUTYLENE GLYCOL; TRIETHOXYCAPRYLYLSILANE; ETHYLHEXYLGLYCERIN; WATER; MEDIUM-CHAIN TRIGLYCERIDES; DIMETHICONE; POLYHYDROXYSTEARIC ACID (2300 MW); FERRIC OXIDE YELLOW; CI 77499; .ALPHA.-TOCOPHEROL ACETATE; PHENOXYETHANOL; ANHYDROXYLITOL; XYLITOL; SIMMONDSIA CHINENSIS (JOJOBA) SEED OIL; NEOPENTYL GLYCOL DIETHYLHEXANOATE; PRUNUS AMYGDALUS DULCIS (SWEET ALMOND) OIL; CI 77491; SODIUM OLIVATE; VANILLA PLANIFOLIA FRUIT OIL; CITRIC ACID; JASMINUM GRANDIFLORUM FLOWER; XYLITYLGLUCOSIDE

Volition Beauty (as PLD): Getaway Glow SPF 30 Radiant Sunscreen (72577-101)

ACTIVE INGREDIENT

ZINC OXIDE 10%

PURPOSE

SUNSCREEN

USE

- HELPS PREVENT SUNBURN

WARNINGS

- FOR EXTERNAL USE ONLY.

- DO NOT USE ON DAMAGED OR BROKEN SKIN.

- WHEN USING THIS PRODUCT KEEP OUT OF EYES. RINSE WITH WATER TO REMOVE.

- STOP USE AND ASK A DOCTOR IF RASH OCCURS.

- KEEP OUT OF REACH OF CHILDREN. IF SWALLOWED, GET MEDICAL HELP OR CONTACT A POISON CONTROL CENTER RIGHT AWAY.

DIRECTIONS

- APPLY LIBERALLY 15 MINUTES BEFORE SUN EXPOSURE.
- CHILDREN UNDER 6 MONTHS OF AGE: ASK A DOCTOR.
- USE A WATER-RESISTANT SUNSCREEN IF SWIMMING OR SWEATING.
- REAPPLY AT LEAST EVERY 2 HOURS.
- SUN PROTECTION MEASURES: SPENDING TIME IN THE SUN INCREASES YOUR RISK OF SKIN CANCER AND EARLY SKIN AGING. TO DECREASE THIS RISK, REGULARLY USE A SUNSCREEN WITH A BROAD SPECTRUM SPF VALUE OF 15 OR HIGHER AND OTHER SUN PROTECTION MEASURES INCLUDING:
- LIMIT TIME IN THE SUN, ESPECIALLY FROM 10 A.M. - 2 P.M.
- WEAR LONG-SLEEVED SHIRTS, PANTS, HATS, AND SUNGLASSES.

OTHER INFORMATION

- PROTECT THE PRODUCT IN THIS CONTAINER FROM EXCESSIVE HEAT AND DIRECT SUN.

INACTIVE INGREDIENTS

Water (Aqua), Caprylic/Capric Triglyceride, Butylene Glycol, Diethylhexyl 2,6-Naphthalate, Polyhydroxystearic Acid, Hydroxyethyl Acrylate/Sodium, Acryloyldimethyl Taurate Copolymer, Sodium Olivate, Prunus Amygdalus Dulcis (Sweet Almond) Oil, Simmondsia Chinensis (Jojoba) Seed Oil, Jasminum Grandiflorum (Jasmine) Flower Extract, Vanilla Planifolia Fruit Oil, Tocopheryl Acetate, Xylitol, Xylitylglucoside, Anhydroxylitol, Dimethicone, Neopentyl Glycol Diethylhexanoate, Triethoxycaprylylsilane, Citric Acid, Phenoxyethanol,
Ethylhexylglycerin, Iron Oxides.